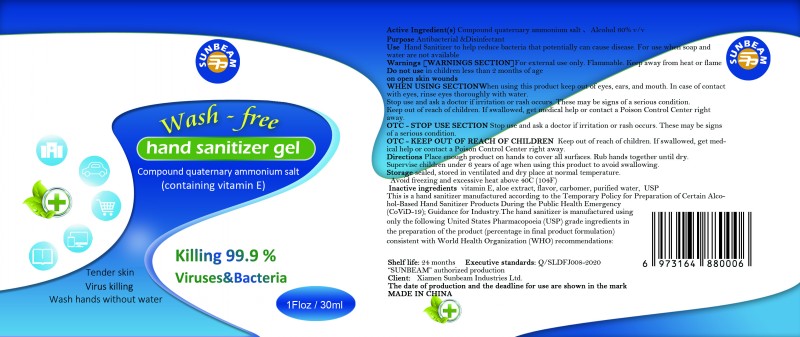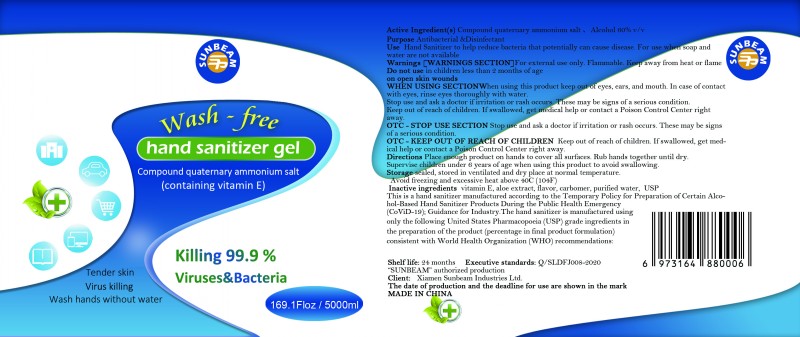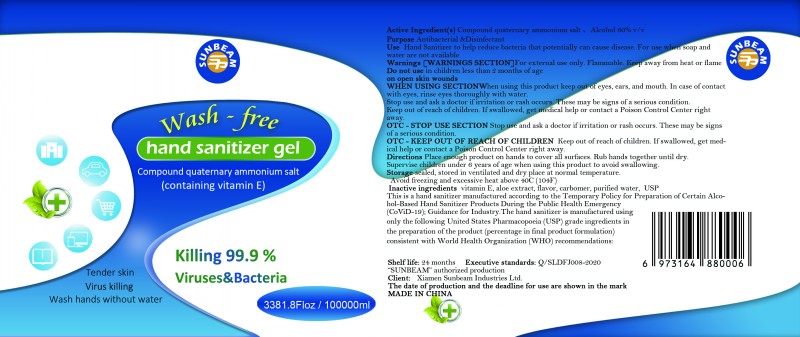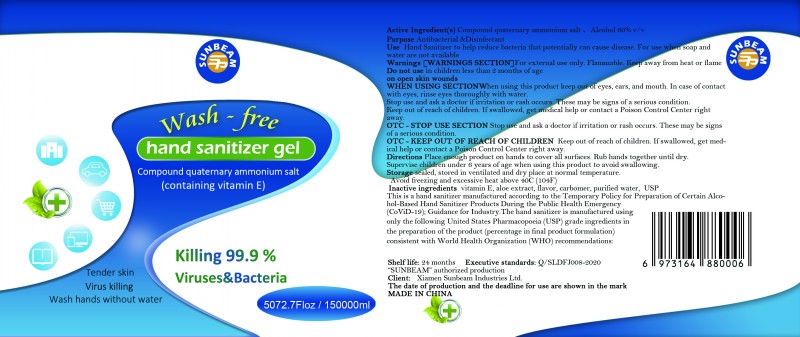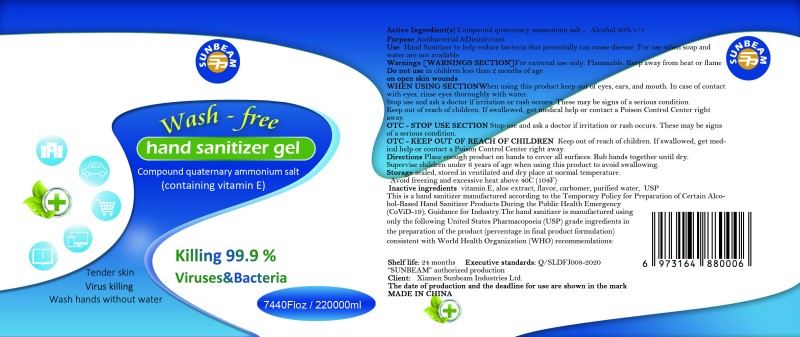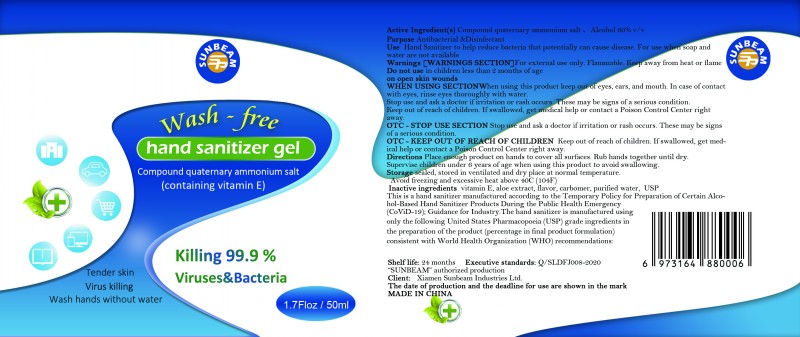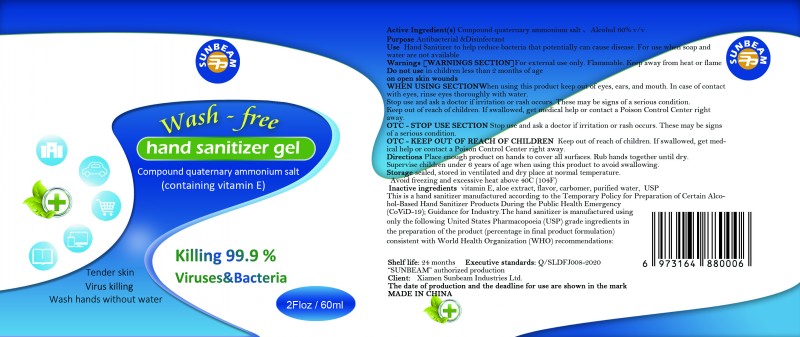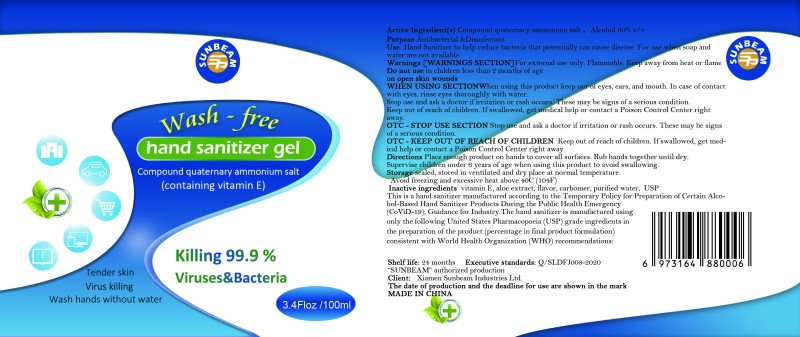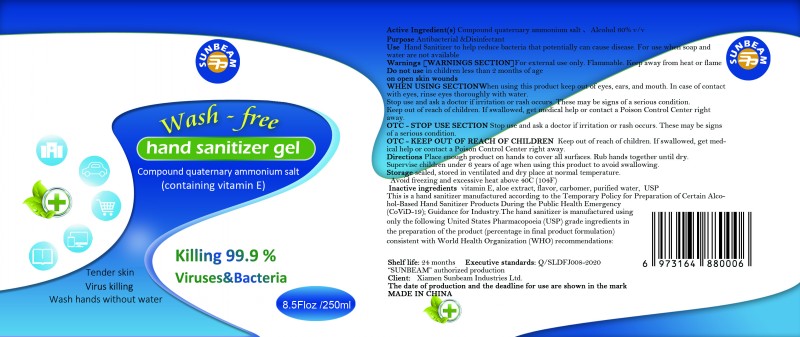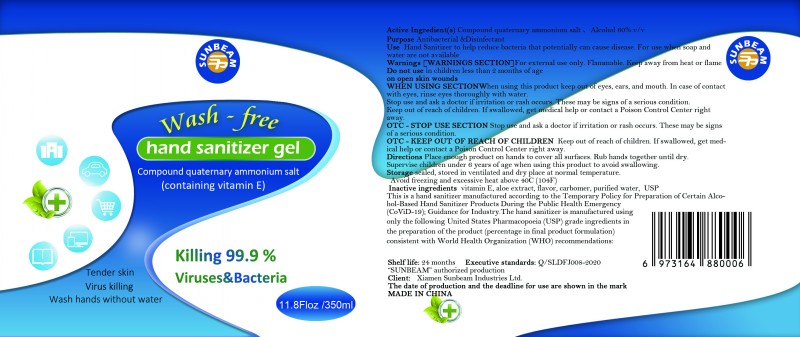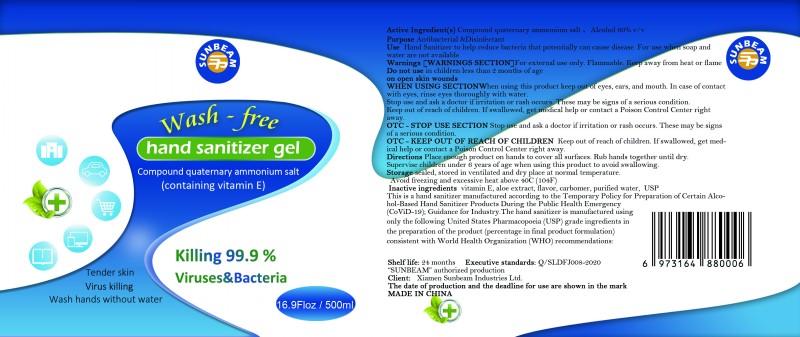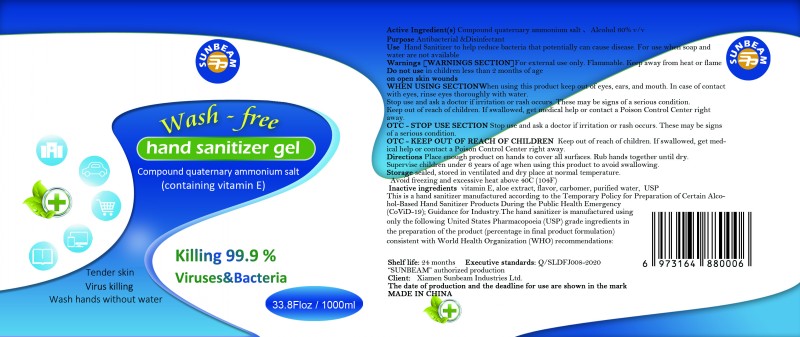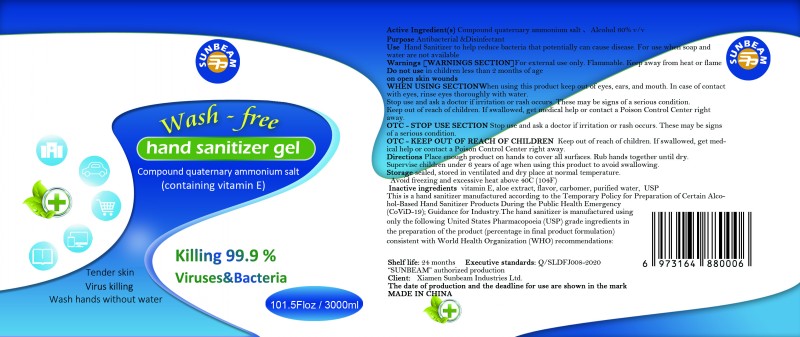 DRUG LABEL: Sunbeam  Wash-Free Hand Sanitizer/Disinfectant
NDC: 78214-001 | Form: GEL
Manufacturer: Xiamen Sunbeam Industries Ltd.
Category: otc | Type: HUMAN OTC DRUG LABEL
Date: 20200518

ACTIVE INGREDIENTS: ALCOHOL 60 mL/100 mL
INACTIVE INGREDIENTS: TOCOPHEROL; ALOE; METHYL SALICYLATE; WATER; CARBOMER HOMOPOLYMER, UNSPECIFIED TYPE

hand sanitizer gel

Active Ingredient(s)

Compound quaternary ammonium salt, Alcohol 60%v/v

Purpose

Antibacterial &Disinfectant

Use

Hand Sanitizer to help reduce bacteria that potentially can cause disease. For use when soap and water are not available

Warnings

For external use only Flammable. Keep away from heat or flame

Do not use

in children less than 2 months of age on open skin wounds

When using this product

keep out of eyes, ears, and mouth. In case of contact with eyes, rinse eyes thoroughly with water.

Stop use and ask a doctor if irritation or rash occurs, These may be signs of a serious condition.

Keep out of reach of children. If swallowed, get medical help or contact a Poison Control Center right away.

Stop use and ask a doctor

if irritation or rash occurs. These may be signs of a serious condition .

Keep out of reach of children

If swallowed, get med-ical help or contact a Poison Control Center right away.

Directions

Place enough product on hands to cover all surfaces. Rub hands together until dry.

Supervise children under 6 years of age when using this product to avoid swallowing.

Other information

Storage sealed, stored in ventilated and dry place at normal temperature.

Avoiding freezing and excessive heat above 40C(104F)

Inactive ingredients

vitamin E, aloe extract, flavor, carbomer, purified water, USP